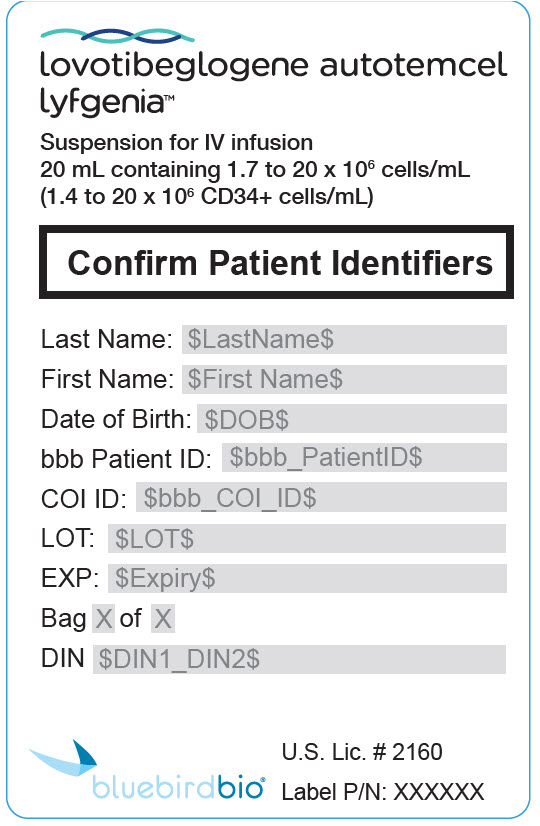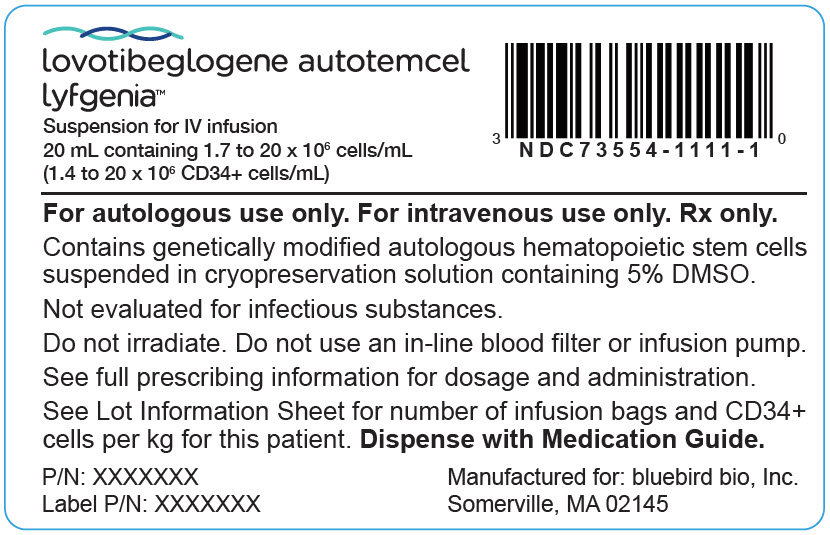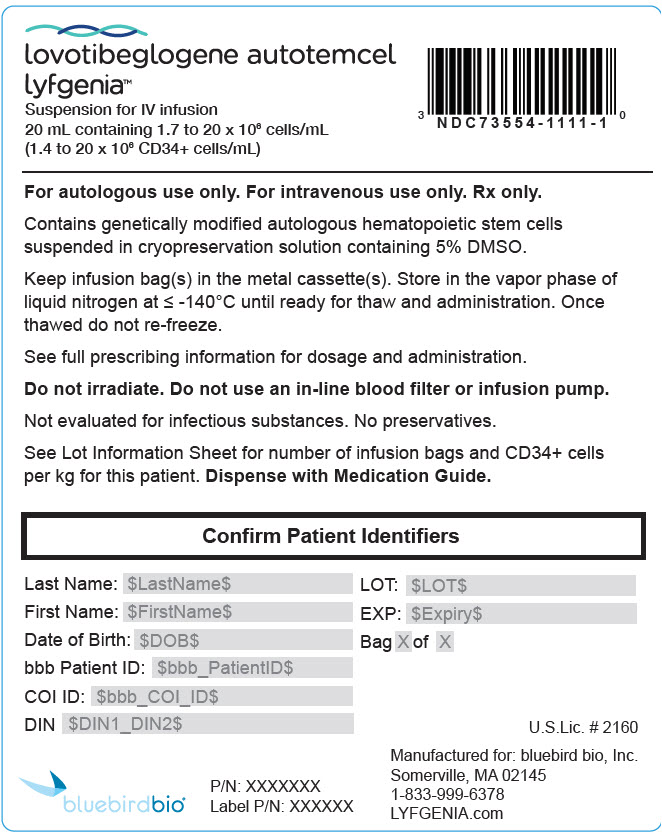 DRUG LABEL: Lyfgenia
NDC: 73554-1111 | Form: SUSPENSION
Manufacturer: Genetix Biotherapeutics Inc.
Category: other | Type: CELLULAR THERAPY
Date: 20251223

ACTIVE INGREDIENTS: lovotibeglogene autotemcel 20000000 1/20 mL

HIGHLIGHTS OF PRESCRIBING INFORMATION

These highlights do not include all the information needed to use LYFGENIA safely and effectively. See full prescribing information for LYFGENIA.
LYFGENIA® (lovotibeglogene autotemcel) suspension for intravenous infusion
Initial U.S. Approval: 2023

WARNING: HEMATOLOGIC MALIGNANCY

See full prescribing information for complete boxed warning.

Hematologic malignancy has occurred in patients treated with LYFGENIA. Monitor patients closely for evidence of malignancy through complete blood counts at least every 6 months and through integration site analysis at Months 6, 12, and as warranted. (5.1)

1 INDICATIONS AND USAGE

LYFGENIA is an autologous hematopoietic stem cell-based gene therapy indicated for the treatment of patients 12 years of age or older with sickle cell disease and a history of vaso-occlusive events. (1)

Limitations of Use

Following treatment with LYFGENIA, patients with α-thalassemia trait (-α3.7/-α3.7) may experience anemia with erythroid dysplasia that may require chronic red blood cell transfusions. LYFGENIA has not been studied in patients with more than two α-globin gene deletions. (1)

2 DOSAGE AND ADMINISTRATION

For autologous use only. For intravenous use only.

- Patients are required to undergo hematopoietic stem cell (HSC) mobilization followed by apheresis to obtain CD34+ cells for LYFGENIA manufacturing. (2.2)
- Dosing of LYFGENIA is based on the number of CD34+ cells in the infusion bag(s) per kg of body weight. (2.1)
- The minimum recommended dose is 3 × 10^6 CD34+ cells/kg. (2.1)
- Myeloablative conditioning must be administered before infusion of LYFGENIA. (2.2)
- Following myeloablative conditioning, allow a minimum of 48 hours of washout before LYFGENIA infusion. (2.2)
- Verify that the patient's identity matches the unique patient identification information on the LYFGENIA infusion bag(s) prior to infusion. (2.2)
- Do not sample, alter, irradiate, or refreeze LYFGENIA. (2.2)
- Do not use an in-line blood filter or an infusion pump. (2.3)
- Administer LYFGENIA within 4 hours after thawing. (2.3)
- Administer each infusion bag of LYFGENIA via intravenous infusion over a period of less than 30 minutes. (2.3)

3 DOSAGE FORMS AND STRENGTHS

LYFGENIA is a cell suspension for intravenous infusion. (3)

A single dose of LYFGENIA contains a minimum of 3 × 10^6 CD34+ cells/kg of body weight, in one to four infusion bags. (3)

4 CONTRAINDICATIONS

None. (4)

5 WARNINGS AND PRECAUTIONS

- Delayed Platelet Engraftment: Monitor patients frequently for thrombocytopenia and bleeding until platelet engraftment and platelet recovery are achieved. (5.2)
- Neutrophil Engraftment Failure: Monitor absolute neutrophil counts (ANC) after LYFGENIA infusion. If neutrophil engraftment does not occur, administer rescue cells. (5.3)
- Insertional Oncogenesis: There is a potential risk of insertional oncogenesis after treatment with LYFGENIA. (5.4)
- Hypersensitivity Reactions: Monitor for hypersensitivity reactions during infusion. (5.5)

6 ADVERSE REACTIONS

Most common adverse reactions ≥ Grade 3 (incidence ≥ 20%) were stomatitis, thrombocytopenia, neutropenia, febrile neutropenia, anemia, and leukopenia. (6.1)

To report SUSPECTED ADVERSE REACTIONS, contact bluebird bio at 1-833-999-6378 or FDA at 1-800-FDA-1088 or www.fda.gov/medwatch.

7 DRUG INTERACTIONS

- Anti-retrovirals: Discontinue anti-retroviral medications at least one month prior to mobilization and until all cycles of apheresis are completed. There are some long-acting anti-retroviral medications that may require a longer duration of discontinuation for elimination of the medication. (7.2)
- Hydroxyurea: Discontinue 2 months prior to mobilization and 2 days prior to conditioning. (7.3)
- Iron chelation: Discontinue at least 7 days prior to mobilization and conditioning. (7.4)

FULL PRESCRIBING INFORMATION

WARNING: HEMATOLOGIC MALIGNANCY

Hematologic malignancy has occurred in patients treated with LYFGENIA. Monitor patients closely for evidence of malignancy through complete blood counts at least every 6 months and through integration site analysis at Months 6, 12, and as warranted [see Warnings and Precautions (5.1)].

1 INDICATIONS AND USAGE

LYFGENIA is indicated for the treatment of patients 12 years of age or older with sickle cell disease and a history of vaso-occlusive events.

Limitations of Use

Following treatment with LYFGENIA, patients with α-thalassemia trait (-α3.7/-α3.7) may experience anemia with erythroid dysplasia that may require chronic red blood cell transfusions [see Adverse Reactions (6.1)]. LYFGENIA has not been studied in patients with more than two α-globin gene deletions.

2 DOSAGE AND ADMINISTRATION

For autologous use only. For one-time single-dose intravenous use only.

2.1 Dose

LYFGENIA is provided as a single dose for infusion containing a suspension of CD34+ cells in one to four infusion bags. The minimum recommended dose of LYFGENIA is 3 × 10^6 CD34+ cells/kg.

See the Lot Information Sheet provided with the product shipment for additional information pertaining to dose.

2.2 Preparation Before LYFGENIA Infusion

Confirm that autologous hematopoietic stem cell (HSC) transplantation is appropriate for the patient before mobilization and apheresis and before myeloablative conditioning are initiated. Perform screening for infectious diseases, specifically human immunodeficiency virus 1 & 2 (HIV-1/HIV-2), in accordance with clinical guidelines before collection of cells for manufacturing. There are no data on use of LYFGENIA in HIV-positive patients.

Prepare for Mobilization and Apheresis

Prepare patients for mobilization with at least 2 cycles of scheduled transfusions (one each month) with erythrocytapheresis being preferred. For at least 60 days prior to mobilization and through myeloablative conditioning, patients should undergo a transfusion regimen to reach a target Hb of 8-10 g/dL, not to exceed 12 g/dL, and HbS of less than 30% to reduce the risk of SCD-related complications. Perform erythrocytapheresis within a recommended 4 days preceding mobilization to reach the target of less than 30% HbS.

Manage other concomitant medications (as applicable) as described below:

- Hydroxyurea: Discontinue at least 2 months prior to mobilization. Patients should not resume hydroxyurea until all cycles of apheresis are completed.
- Disease-modifying agents (e.g., L-glutamine, voxelotor and crizanlizumab): Discontinue at least 2 months prior to mobilization as the interaction between disease modifying agents and mobilization agents is unknown.
- Erythropoietin: Discontinue at least 2 months prior to mobilization.
- Iron chelation: Discontinue at least 7 days prior to mobilization.
- Granulocyte-colony stimulating factor (G-CSF): Do not administer G-CSF prior to or with mobilization agents.
- Anti-retrovirals: Discontinue prophylactic HIV anti-retroviral medications at least one month prior to mobilization and do not resume until all cycles of apheresis are completed. There are some long-acting anti-retroviral medications that may require a longer duration of discontinuation for elimination of the medication.

Mobilization and Apheresis

Perform HSC mobilization followed by apheresis to obtain CD34+ cells for product manufacturing. Administer plerixafor to mobilize stem cells prior to the apheresis procedure at a dose of 0.24 mg/kg/day.^1

Begin apheresis approximately 4 to 6 hours after plerixafor administration. If more than one apheresis day is required, confirm platelet counts to be ≥ 75 × 10^9/L within 24 hours of subsequent apheresis sessions, prior to administration of plerixafor on that day. If platelet counts do not meet these criteria, defer mobilization and apheresis until the platelet counts recover to ≥ 75 × 10^9/L. For patients undergoing more than 1 mobilization cycle, separate each cycle by at least 14 days. Administer daily plerixafor 4 to 6 hours prior to each apheresis collection. If a sufficient number of cells are collected after the first mobilization cycle, no further mobilization/apheresis is required. In clinical studies, the minimum number of CD34+ cells to manufacture LYFGENIA was collected in most patients with 1 or 2 cycles of mobilization and apheresis which typically required 2 consecutive collection days per cycle.

Maximize CD34+ cell collection to obtain as many CD34+ stem cells as possible for product manufacturing during each mobilization and apheresis cycle. Target a minimum collection of 16.5 × 10^6 CD34+ cells/kg for manufacturing and back-up. If, after manufacturing, the minimum dose of 3 × 10^6 CD34+ cells/kg is not achieved, the patient may undergo additional cycles of mobilization and apheresis, separated by at least 14 days, to obtain more cells for additional manufacture. Multiple drug product lots may be administered to comprise the final dose.

Retain ≥ 1.5 × 10^6 CD34+ cells/kg from the collection for back-up. These cells must be collected from the patient and be cryopreserved prior to myeloablative conditioning. The back-up collection may be needed for rescue treatment if there is: 1) compromise of hematopoietic stem cells or LYFGENIA before infusion, 2) primary engraftment failure, or 3) loss of engraftment after infusion with LYFGENIA.

Manage concomitant medications (as applicable) between apheresis and conditioning as described below:

- Transfusions: Scheduled transfusions can be continued between apheresis and conditioning. Patients should maintain total hemoglobin (Hb) levels of 8 to 10 g/dL. Hb levels should not exceed 12 g/dL. A scheduled transfusion should be performed within 2 days prior to conditioning.
- Hydroxyurea: If administered after apheresis, discontinue hydroxyurea at least 2 days prior to myeloablative conditioning.
- Disease-modifying agents (e.g., L-glutamine, voxelotor and crizanlizumab): Discontinue disease modifying agents at least 2 months prior to conditioning as the interaction between disease modifying agents and conditioning agents are unknown.
- Iron chelation: If administered after apheresis, discontinue iron chelation at least 7 days prior to myeloablative conditioning.
- G-CSF: Do not administer G-CSF between mobilization and conditioning.
- Anti-retrovirals and erythropoietin: There are no data regarding use of anti-retrovirals or erythropoietin between apheresis and conditioning.

Myeloablative Conditioning

Do not begin myeloablative conditioning until the complete set of infusion bag(s) constituting the dose of LYFGENIA has been received and stored at the treatment center and the availability of the back-up collection is confirmed.

Myeloablative conditioning with busulfan must be administered before infusion of LYFGENIA.

Busulfan should be administered via a central venous line. For patients weighing less than 35 kg, administer every 6 hours; for patients weighing 35 kg or more, busulfan can be administered either once daily or every 6 hours. Calculate the dose on the basis of the lower of the ideal versus actual body weight.

The recommended initial dose of busulfan is 3.2 mg/kg/day for 4 consecutive days as a 3-hour infusion for a total of 4 doses.^2 To achieve myeloablation, the busulfan target AUC is 5000 (range 4400 to 5400) μM*min for a once daily dosing regimen.

For divided dosing, initial dose of busulfan is 0.8 mg/kg/dose every 6 hours as a 2-hour infusion for 16 consecutive doses. Target AUC is 1250 (range 1100 to 1350) μM*min for a q6h dosing regimen.

Perform pharmacokinetic (PK) monitoring after the first dose and adjust dose to achieve the target AUC. Adjust sample collection based on whether a 2-hour or 3-hour infusion is used. If feasible, daily busulfan PK measurement is recommended.

Administer seizure prophylaxis with agents other than phenytoin at least 12 hours prior to initiating busulfan. Do not use phenytoin because of its induction of cytochrome P450 and resultant increased clearance of busulfan.

Consider prophylaxis for hepatic veno-occlusive disease (VOD)/hepatic sinusoidal obstruction syndrome with ursodeoxycholic acid or defibrotide.

After completion of the myeloablative conditioning, allow a minimum of 48 hours of washout before LYFGENIA infusion.

Receipt and Storage of LYFGENIA

- LYFGENIA is shipped in the vapor phase of liquid nitrogen shipper.
- Confirm patient identifiers on the product label(s) and Lot Information Sheet within the shipper.
- If there are any concerns about the product or packaging upon receipt, contact bluebird bio at 1-833-999-6378.
- Keep the infusion bag(s) in the metal cassette(s) and transfer LYFGENIA from the vapor phase of liquid nitrogen shipper to the treatment center vapor phase of liquid nitrogen storage at ≤ -140°C (-220°F). Store in the vapor phase of liquid nitrogen at ≤ -140°C (-220°F) until ready for thaw and administration.

Preparation of LYFGENIA for Infusion

Coordinate the timing of LYFGENIA thaw and infusion. Confirm the infusion time in advance and adjust the start time of LYFGENIA thaw such that it will be available for infusion when the patient and healthcare providers are ready. Note that each infusion bag must be completely administered within 4 hours after thawing.

1. Remove each metal cassette from liquid nitrogen storage and remove each infusion bag from the metal cassette.
2. Confirm that LYFGENIA is printed on the infusion bag(s).
3. Confirm that patient identity matches the unique patient identifiers located on the LYFGENIA infusion bag(s). Do not infuse LYFGENIA if the information on the patient-specific label on the infusion bag does not match the intended patient and contact bluebird bio at 1-833-999-6378.
4. Ensure the correct number of infusion bags are present. Use the accompanying Lot Information Sheet to confirm that each infusion bag is within the expiration date.
5. Inspect each infusion bag for any breaches of integrity before and after thawing and before infusion. If an infusion bag is compromised, follow the local guidelines and contact bluebird bio immediately at 1-833-999-6378.
6. If more than one infusion bag is provided, thaw and administer each infusion bag completely before proceeding to thaw the next infusion bag. Maintain any additional infusion bag(s), if applicable, at less than or equal to -140°C (-220°F) until time to thaw.
7. Thaw LYFGENIA at 37°C (98.6°F) in a water bath or dry bath. Thawing of each infusion bag takes approximately 2 to 4 minutes. Do not leave LYFGENIA unattended. Do not submerge the infusion ports in a water bath.
8. After thaw, mix the contents gently by massaging the infusion bag to disperse clumps of cellular material until all of the contents are uniform. If visible cell clumps remain, continue to gently mix the contents of the bag. Most small clumps of cellular material should disperse with gentle manual mixing. Do not filter, wash, spin down and/or resuspend LYFGENIA in new media prior to infusion.
9. Do not sample, alter, irradiate or refreeze LYFGENIA.

2.3 Administration

LYFGENIA is for autologous use only. The patient's identity must match the patient identifiers on the LYFGENIA cassette(s) and infusion bag(s). Do not infuse LYFGENIA if the information on the patient-specific label does not match the intended patient.

- Administer LYFGENIA within 4 hours after thawing.
- Do not use an in-line blood filter or an infusion pump.

1. Before infusion, confirm that the patient's identity matches the unique patient identifiers on the LYFGENIA infusion bag(s). Use the Lot Information Sheet to confirm the total number of infusion bags to be administered.
2. Expose the sterile port on the infusion bag by tearing off the protective wrap covering the port.
3. Infuse LYFGENIA as soon as possible after thawing and complete the infusion within 4 hours.
4. Administer each infusion bag of LYFGENIA via intravenous infusion over a period of less than 30 minutes. If more than one infusion bag is provided, administer the contents of each infusion bag completely before proceeding to thaw and infuse the contents of the next infusion bag.
5. Administer the entire contents of each infusion bag to ensure that as many cells as possible are infused into the patient. After administration of each drug product, the infusion bag and any associated tubing are flushed with at least 50 mL of 0.9% sodium chloride solution to ensure as many cells as possible are infused into the patient.

After LYFGENIA Administration

Standard procedures for patient management after HSC transplantation should be followed after LYFGENIA infusion.

- Irradiate any blood products required for at least the first 3 months after LYFGENIA infusion and per transplant physician's recommendation.
- There is no experience regarding the use of hydroxyurea, anti-retrovirals, erythropoietin or disease-modifying agents, such as voxelotor or crizanlizumab, after LYFGENIA infusion.
- Avoid use of myelosuppressive iron chelators for 6 months. If iron chelation is needed, consider administration of non-myelosuppressive iron chelators. Phlebotomy can be used in lieu of iron chelation when appropriate.
- G-CSF is not recommended for 21 days after LYFGENIA infusion.
- Patients should not donate blood, organs, tissues, or cells at any time in the future.

LYFGENIA contains human blood stem cells that are genetically modified with a replication-incompetent, self-inactivating lentiviral vector (LVV). Follow universal precautions and local biosafety guidelines (Biosafety Level 2) for handling and disposal of LYFGENIA to avoid potential transmission of infectious diseases.

3 DOSAGE FORMS AND STRENGTHS

LYFGENIA is a cell suspension for intravenous infusion.

LYFGENIA is composed of one to four infusion bags which contain 1.7 to 20 × 10^6 cells/mL suspended in cryopreservation solution [see How Supplied/Storage and Handling (16)]. Each infusion bag contains approximately 20 mL of LYFGENIA. A single dose of LYFGENIA contains a minimum of 3 × 10^6 CD34+ cells per kg of body weight, suspended in cryopreservation solution.

See the Lot Information Sheet for actual dose.

4 CONTRAINDICATIONS

None.

5 WARNINGS AND PRECAUTIONS

5.1 Hematologic Malignancy

Hematologic malignancy has occurred in patients treated with LYFGENIA (Study 1, Group A). At the time of initial product approval, two patients treated with an earlier version of LYFGENIA using a different manufacturing process and transplant procedure (Study 1, Group A) developed acute myeloid leukemia (AML). One patient with α-thalassemia trait (Study 1, Group C) has been diagnosed with myelodysplastic syndrome (MDS) [see Adverse Reactions (6.1)].

The additional hematopoietic stress associated with mobilization, conditioning, and infusion of LYFGENIA, including the need to regenerate the hematopoietic system, may increase the risk of a hematologic malignancy.

Patients with sickle cell disease have an increased risk of hematologic malignancy as compared to the general population.^(3, 4) Patients treated with LYFGENIA may develop hematologic malignancies and should have lifelong monitoring. Monitor for hematologic malignancies with a complete blood count (with differential) at least every 6 months for at least 15 years after treatment with LYFGENIA, and integration site analysis at Months 6, 12, and as warranted.

In the event that a malignancy occurs, contact bluebird bio at 1-833-999-6378 for reporting and to obtain instructions on collection of samples for testing.

Post-Marketing Long Term Follow-Up Study

Patients who intend to receive treatment with LYFGENIA are encouraged to enroll in the study, as available, to assess the long-term safety of LYFGENIA and the risk of malignancies occurring after treatment with LYFGENIA by calling bluebird bio at 1-833-999-6378. The study includes monitoring (at pre-specified intervals) for clonal expansion.

5.2 Delayed Platelet Engraftment

Delayed platelet engraftment has been observed with LYFGENIA. Bleeding risk is increased prior to platelet engraftment and may continue after engraftment in patients with prolonged thrombocytopenia. Two patients (4%) required more than 100 days post treatment with LYFGENIA to achieve platelet engraftment [see Adverse Reactions (6.1)].

Patients should be made aware of the risk of bleeding until platelet recovery has been achieved. Monitor patients for thrombocytopenia and bleeding according to standard guidelines. Conduct frequent platelet counts until platelet engraftment and platelet recovery are achieved. Perform blood cell count determination and other appropriate testing whenever clinical symptoms suggestive of bleeding arise.

5.3 Neutrophil Engraftment Failure

There is a potential risk of neutrophil engraftment failure after treatment with LYFGENIA. Neutrophil engraftment failure is defined as failure to achieve three consecutive absolute neutrophil counts (ANC) ≥ 0.5 × 10^9 cells/L obtained on different days by Day 43 after infusion of LYFGENIA. Monitor neutrophil counts until engraftment has been achieved. If neutrophil engraftment failure occurs in a patient treated with LYFGENIA, provide rescue treatment with the back-up collection of CD34+ cells [see Adverse Reactions (6.1)].

5.4 Insertional Oncogenesis

There is a potential risk of lentiviral vector-mediated insertional oncogenesis after treatment with LYFGENIA.

5.5 Hypersensitivity Reactions

Allergic reactions may occur with the infusion of LYFGENIA. The dimethyl sulfoxide (DMSO) or dextran 40 in LYFGENIA may cause hypersensitivity reactions, including anaphylaxis.

5.6 Anti-retroviral Use

Patients should not take prophylactic HIV anti-retroviral medications for at least one month prior to mobilization and until all cycles of apheresis are completed. There are some long-acting anti-retroviral medications that may require a longer duration of discontinuation for elimination of the medication [see Dosing and Administration (2.2) and Drug Interactions (7.2)].

If a patient is taking anti-retrovirals for HIV prophylaxis, confirm a negative test for HIV before beginning mobilization and apheresis of CD34+ cells.

5.7 Hydroxyurea Use

Patients should not take hydroxyurea for at least 2 months prior to mobilization and until all cycles of apheresis are completed. If hydroxyurea is administered between mobilization and conditioning, discontinue 2 days prior to initiation of conditioning [see Dosing and Administration (2.2) and Drug Interactions (7.3)].

5.8 Iron Chelation

Do not administer myelosuppressive iron chelators for 6 months post-treatment with LYFGENIA[see Dosing and Administration (2.2) and Drug Interactions (7.4)].

5.9 Interference with PCR-based Testing

Patients who have received LYFGENIA are likely to test positive by polymerase chain reaction (PCR) assays for HIV due to integrated BB305 LVV proviral DNA, resulting in a possible false-positive PCR assay test result for HIV. Therefore, patients who have received LYFGENIA should not be screened for HIV infection using a PCR-based assay.

6 ADVERSE REACTIONS

The following adverse reactions are described elsewhere in the labeling:

- Hematologic Malignancy [see Warnings and Precautions (5.1)]
- Delayed Platelet Engraftment [see Warnings and Precautions (5.2)]
- Neutrophil Engraftment Failure [see Warnings and Precautions (5.3)]
- Insertional Oncogenesis [see Warnings and Precautions (5.4)]
- Hypersensitivity Reactions [see Warnings and Precautions (5.5)]

6.1 Clinical Trials Experience

Because clinical trials are conducted under widely varying conditions, adverse reaction rates observed in the clinical trials of a drug cannot be directly compared to rates in the clinical trials of another drug and may not reflect the rates observed in practice.

Safety was based on patients with sickle cell disease in one open-label, single-arm clinical trial and one long-term follow-up study. Of the 54 patients who initiated stem cell collection, the median (min, max) age across the studies was 25 (12, 43) years, 63% were males, 89% were Black or African American, 2% were Asian, 2% White/Caucasian and 4% were not reported. The median (min, max) duration of follow-up was 42 (12, 87) months.

Mobilization and apheresis triggered SAEs of sickle cell crisis in 6 (14%, 6/44) patients who initiated mobilization in the intent-to-treat population.

All patients who initiated conditioning (100%, 45/45) experienced at least one adverse event attributed to conditioning. The majority of conditioning-attributed events were non-serious and were consistent with the known effects of alkylating agents.

Thirty-three (73%, 33/45) patients who received LYFGENIA experienced at least one serious adverse event (SAE). Most SAEs were related to conditioning or underlying disease.

Table 1 presents the adverse drug reactions following treatment with LYFGENIA (Day 1) to Month 24.

Table 1: Adverse Reactions ≥ Grade 3 (> 5%) Following Treatment with LYFGENIA from Day 1 to Month 24 (N = 45) [Includes adverse events associated with busulfan myeloablative conditioning and underlying sickle cell disease.]
Adverse Reaction | Grade 3 or Higher n (%)
Blood and lymphatic system disorders | --
Thrombocytopenia | 31 (69)
Neutropenia | 27 (60)
Febrile neutropenia | 20 (44)
Anemia [Includes a patient with α-thalassemia trait who was diagnosed with myelodysplastic syndrome after Month 24.] | 15 (33)
Leukopenia | 15 (33)
Sickle cell anemia with crisis [Includes events prior to Month 6 and non-adjudicated occurrences.] | 7 (16)
Gastrointestinal disorders | --
Stomatitis | 32 (71)
Nausea | 4 (9)
General disorders and administration site conditions | --
Pyrexia | 3 (7)
Infections and infestations | --
Bacteremia | 3 (7)
Investigations | --
Aspartate aminotransferase increased | 8 (18)
Alanine aminotransferase increased | 6 (13)
Gamma-glutamyl transferase increased | 6 (13)
Blood bilirubin increased | 3 (7)
Metabolism and nutrition disorders | --
Decreased appetite | 5 (11)
Respiratory, thoracic, and mediastinal disorders | --
Pharyngeal inflammation | 5 (11)

Three patients died during LYFGENIA clinical trials; one from sudden cardiac death due to underlying disease and two from acute myeloid leukemia who were treated with an earlier version of LYFGENIA using a different manufacturing process and transplant procedure (Study 1, Group A).

Anemia

Two patients developed anemia following LYFGENIA treatment; one patient continues to require monthly packed red blood cell (pRBC) transfusions. The other patient has been diagnosed with MDS. Both subjects had α-thalassemia trait (-α3.7 /-α3.7) [see Limitations of Use (1)].

Infusion-related reactions to LYFGENIA

Pre-medication for infusion reactions was managed at physician discretion. Infusion-related reactions to LYFGENIA were observed in 2 patients on the day of LYFGENIA infusion. Both infusion-related reactions resolved and were Grade 1. Events included hot flush and decreased diastolic blood pressure.

Platelet engraftment delay

Platelet engraftment, defined as having 3 consecutive platelet values ≥ 50 × 10^9/L obtained on different days after the initial post-transplant nadir without receiving any platelet transfusions for 7 days immediately preceding and during the evaluation period, was achieved in all patients (median [min, max] Day 37 [19, 235]) after LYFGENIA infusion. Two patients treated with LYFGENIA achieved platelet engraftment after Day 100; one of these patients was administered eltrombopag until Day 234 [see Warnings and Precautions (5.2)].

Neutrophil engraftment

All patients achieved neutrophil engraftment. Neutrophil engraftment, defined as having 3 consecutive ANC laboratory values ≥ 0.5 × 10^9 cells/L obtained on 3 different days by Day 43, was reported on median (min, max) Day 20 (12, 35) after LYFGENIA infusion.

7 DRUG INTERACTIONS

No formal drug interaction studies have been performed. LYFGENIA is not expected to interact with the hepatic cytochrome P-450 family of enzymes or drug transporters.

7.1 Live Vaccines

Follow institutional guidelines for vaccine administration. The safety of immunization with live viral vaccines during or following LYFGENIA treatment has not been studied. Recommendations for vaccination schedules should be followed as per guidelines post-autologous hematopoietic stem cell transplant and functional asplenia.

7.2 Anti-retrovirals

Patients should not take anti-retroviral medications for at least one month prior to mobilization for required and until all cycles of apheresis are completed [see Warnings and Precautions (5.6)]. There are some long-acting anti-retroviral medications that may require a longer duration of discontinuation for elimination of the medication. Anti-retroviral medications may interfere with manufacturing of LYFGENIA.

7.3 Hydroxyurea

Patients should not take hydroxyurea for at least 2 months prior to mobilization and until all cycles of apheresis are completed and should discontinue 2 days prior to initiation of conditioning [see Warnings and Precautions (5.7)].

7.4 Iron Chelation

Drug-drug interactions between iron chelators and the mobilization process and myeloablative conditioning agent must be considered. Iron chelators should be discontinued at least 7 days prior to initiation of mobilization or conditioning. Myelosuppressive iron chelators (e.g., deferiprone) should be restarted no sooner than 6 months after LYFGENIA infusion [see Warnings and Precautions (5.8)]. Non-myelosuppressive iron chelation should be restarted no sooner than 3 months after LYFGENIA infusion. Phlebotomy can be used in lieu of iron chelation, when appropriate.

8 USE IN SPECIFIC POPULATIONS

8.1 Pregnancy

Risk Summary

There are no available data on LYFGENIA administration in pregnant women. Consider the risks associated with myeloablative conditioning agents on pregnancy and fertility.

No reproductive and developmental toxicity studies in animals have been conducted with LYFGENIA to assess whether it can cause fetal harm when administered to a pregnant woman. It is not known whether LYFGENIA has the potential to be transferred to the fetus. Therefore, LYFGENIA should not be administered to women who are pregnant, and pregnancy after LYFGENIA infusion should be discussed with the treating physician.

In the U.S. general population, the estimated background risk of major birth defects and miscarriage in clinically recognized pregnancies is 2%-4% and 15%-20%, respectively.

8.2 Lactation

Risk Summary

There is no information regarding the presence of LYFGENIA in human milk, the effect on the breastfed infant, and the effects on milk production. The developmental and health benefits of breastfeeding should be considered along with the mother's clinical need for LYFGENIA and any potential adverse effects on the breastfed child from LYFGENIA. Therefore, LYFGENIA is not recommended for women who are breastfeeding, and breastfeeding after LYFGENIA infusion should be discussed with the treating physician.

8.3 Females and Males of Reproductive Potential

Pregnancy Testing

A negative serum pregnancy test must be confirmed prior to the start of mobilization and re‑confirmed prior to conditioning procedures and before LYFGENIA administration.

Contraception

There are insufficient exposure data to provide a precise recommendation on duration of contraception following treatment with LYFGENIA.

Women of childbearing potential and men capable of fathering a child should use an effective method of contraception (intra-uterine device or combination of hormonal and barrier contraception) from start of mobilization through at least 6 months after administration of LYFGENIA. Advise patients of the risks associated with conditioning agents.

Infertility

There are no data on the effects of LYFGENIA on fertility.

Data are available on the risk of infertility with myeloablative conditioning. Advise patients of the risks and the options for fertility preservation.

8.4 Pediatric Use

The safety and efficacy of LYFGENIA have been established in pediatric patients 12 years of age and older with sickle cell disease, including 8 adolescents (age 12 years to less than 18) [see Clinical Studies (14)].

No clinically meaningful differences in efficacy or safety were observed between the adult and pediatric subgroups.

The safety and efficacy of LYFGENIA in children less than 12 years of age have not been established. No data are available.

8.5 Geriatric Use

LYFGENIA has not been studied in patients 65 years of age and older. Autologous hematopoietic stem cell (HSC) transplantation must be appropriate for a patient to be treated with LYFGENIA.

8.6 Patients Seropositive for Human Immunodeficiency Virus (HIV)

LYFGENIA has not been studied in patients with HIV-1 or HIV-2. A negative serology test for HIV is necessary prior to apheresis. Patients with a positive test for HIV will not be accepted for LYFGENIA treatment.

8.7 Renal Impairment

LYFGENIA has not been studied in patients with renal impairment (defined as creatinine clearance ≤ 70 mL/min/1.73 m^2). Patients' renal function should be assessed for renal impairment to ensure autologous HSC transplantation is appropriate.

8.8 Hepatic Impairment

LYFGENIA has not been studied in patients with advanced hepatic disease. Patients' hepatic function should be assessed for hepatic impairment to ensure autologous HSC transplantation is appropriate.

11 DESCRIPTION

LYFGENIA (lovotibeglogene autotemcel) is a βA-T87Q-globin gene therapy consisting of autologous CD34+ cells from patients with sickle cell disease containing hematopoietic stem cells (HSCs) transduced with BB305 LVV encoding βA-T87Q-globin, suspended in cryopreservation solution. LYFGENIA is intended for one-time administration to add functional copies of a modified form of the β-globin gene (βA-T87Q-globin gene) into the patient's own HSCs.

LYFGENIA is prepared using the patient's own HSCs, which are collected via apheresis procedure(s). The autologous cells are enriched for CD34+ cells, then transduced ex vivo with BB305 LVV. The promoter, a regulatory element that controls the expression of the transgene selected for BB305 LVV, is a cellular (non-viral) promoter that controls gene expression specific to the erythroid lineage cells (red blood cells and their precursors). BB305 LVV encodes βA-T87Q-globin.

The transduced CD34+ cells are washed, formulated into a suspension, and then cryopreserved. LYFGENIA is frozen in a patient-specific infusion bag(s) and is thawed prior to administration [see Dosage and Administration (2.2), How Supplied/Storage and Handling (16)]. The thawed product is colorless to white to red, including shades of white or pink, light yellow, and orange, and may contain small proteinaceous particles. Due to the presence of cells, the solution may be clear to slightly cloudy and may contain visible cell aggregates.

The formulation contains 5% dimethyl sulfoxide (DMSO).

12 CLINICAL PHARMACOLOGY

12.1 Mechanism of Action

LYFGENIA adds functional copies of a modified βA-globin gene (threonine [T] replaced with glutamine [Q] at position 87, T87Q or βA-T87Q-globin) into patients' hematopoietic stem cells (HSCs) through transduction of autologous CD34+ cells with BB305 LVV. After LYFGENIA infusion, the transduced CD34+ HSCs engraft in the bone marrow and differentiate to produce red blood cells containing biologically active βA-T87Q-globin that will combine with α-globin to produce functional Hb containing βA-T87Q-globin (HbAT87Q). βA-T87Q-globin can be distinguished from wildtype βA-globin and from βS-globin through reverse-phase high-performance liquid chromatography (RPHPLC) or ultra-high performance liquid chromatography (UPLC). HbAT87Q has similar oxygen-binding affinity and oxygen hemoglobin dissociation curve to wild type HbA, reduces intracellular and total hemoglobin S (HbS) levels, and is designed to sterically inhibit polymerization of HbS thereby limiting the sickling of red blood cells.

12.2 Pharmacodynamics

HbAT87Q generally increased steadily after LYFGENIA infusion and stabilized by approximately Month 6 after infusion. Patients had a Month 6 median (min, max) HbAT87Q of 5.2 (2.6, 8.8) g/dL in an ongoing Phase 1/2 Study Group C (Study 1-C) (N = 33). HbAT87Q remained durable with a median (min, max) of 5.5 (2.4, 9.4) g/dL at Month 24 (N = 34). HbAT87Q comprised a median (min, max) 45.7 (26.9, 63.2) (N = 34) percent of total non-transfused Hb at Month 24.

Expression of HbAT87Q continued to remain durable through Month 48 (N = 10), demonstrating sustained expression of the βA-T87Q protein derived from irreversible integration of the βA-T87Q-globin gene into long-term hematopoietic stem cells (HSCs).

12.3 Pharmacokinetics

LYFGENIA is an autologous gene therapy which includes hematopoietic stem cells (HSCs) that have been genetically modified ex vivo. The nature of LYFGENIA is such that conventional studies on pharmacokinetics, absorption, distribution, metabolism, and elimination are not applicable.

13 NONCLINICAL TOXICOLOGY

13.1 Carcinogenesis, Mutagenesis, Impairment of Fertility

No carcinogenicity studies have been performed with LYFGENIA.

No studies have been conducted to evaluate the effects of LYFGENIA on fertility.

14 CLINICAL STUDIES

The efficacy of LYFGENIA was studied in a single-arm, 24-month, open-label, multicenter Phase 1/2 study (Study 1-C) and continued on a long-term follow-up study. In Study 1-C, 43 subjects underwent apheresis after mobilization with plerixafor of which 36 patients received myeloablative busulfan conditioning. Seven patients did not proceed to conditioning; 2 patients discontinued due to apheresis-related issues and 5 discontinued at patient and/or physician discretion.

Thirty-six patients received the intravenous infusion of LYFGENIA with a median (min, max) dose of 6.4 (3, 14) × 10^6 CD34+ cells/kg (48 hours after the last dose of busulfan). (See Section 2 for Dosage and Administration for Mobilization and Apheresis and Myeloablative Conditioning.)

As LYFGENIA is an autologous therapy, prophylactic long-term immunosuppressive agents were not required in clinical studies. No patients experienced graft failure or graft rejection. (See Section 6 for details of neutrophil and platelet engraftment.)

Table 2 includes the demographics and baseline characteristics for patients in Study 1-C.

Table 2: Demographics and Characteristics for Patients Treated with LYFGENIA in Study 1-C
 | Transplant Population | Transplant Population for VOE Efficacy Outcomes
Attribute | N = 36 | N = 32
β-globin Genotype: βS/βS, n (%) | 36 (100) | 32 (100)
α-globin Genotype: αα/αα, n (%) | 23 (64) | 20 (63)
α-globin Genotype: αα/-α3.7, n (%) | 11 (31) | 10 (31)
α-globin Genotype: -α3.7/-α3.7, n (%) | 2 (6) | 2 (6)
Age in years, median (min, max) | 24 (12, 38) | 25 (12, 38)
Age in years, n (%)
≥ 18 years | 28 (78) | 24 (75)
≥ 12 years to < 18 | 8 (22) | 8 (25)
Sex: Male, n (%) | 22 (61) | 20 (63)
Race: Black/African American n (%) | 35 (97) | 31 (97)
Race: Not Reported n (%) | 1 (3) | 1 (3)
Patients with History of Stroke [Patients with a history of stroke were included in early inclusion criteria in Study 1-C.] , n (%) | 5 (14) | 1 (3)

Efficacy Outcomes

The transplant population for VOE efficacy outcomes included patients with a history of at least 4 VOEs in the 24 months prior to informed consent. The efficacy outcomes were complete resolution of VOEs (VOE-CR) and severe VOEs (sVOE-CR) between 6 months and 18 months after infusion of LYFGENIA.

VOEs were defined as any of the following events requiring evaluation at a medical facility:

- an episode of acute pain with no medically determined cause other than vaso-occlusion, lasting more than 2 hours
- acute chest syndrome (ACS)
- acute hepatic sequestration
- acute splenic sequestration

Severe VOE (sVOE) were defined as either of the following events:

- VOE requiring a hospitalization or multiple visits to an emergency department/urgent care over 72 hours and receiving intravenous medications at each visit
- priapism requiring any level of medical attention

Table 3: Summary of VOE Efficacy Outcomes for Patients in Study 1-C
Clinical Attribute | Results
VOE-CR
n/N (%) | 28/32 (88%)
[95% CI] | [71, 97]
sVOE-CR
n/N (%) | 30/32 (94%)
[95% CI] | [79, 99]
(s)VOE-CR = elimination of (s)VOEs between 6 and 18 months post infusion with LYFGENIA.

Globin response (GR) was defined as meeting the following criteria for a continuous period of at least 6 months after drug product infusion:

- weighted average hemoglobin AT87Q percentage of non-transfused total Hb ≥ 30% AND
- weighted average non-transfused total Hb (HbS+HbF+HbA2+HbAT87Q) increase of ≥ 3 g/dL compared to baseline total Hb OR weighted average non-transfused total Hb ≥ 10 g/dL.

All 36 patients infused in Study 1-C (transplant population) were evaluated for globin response. 31/36 (86%) achieved GR. All patients maintained GR once it was achieved.

The median (min, max) duration of follow-up for the patients in Study 1-C (N = 36) is 38 (12, 61) months post LYFGENIA infusion. After the primary evaluation period to last follow-up, 4 of 32 patients who achieved VOE-CR experienced VOEs while maintaining GR. After the primary evaluation period up to 24 months, 17 of 35 (49%) patients were prescribed opioids for sickle cell and non-sickle cell-related pain.

Neurologic outcome

Five patients with history of stroke or vasculopathy were treated on Study 1-C. All were at least 18 years old and on chronic transfusion therapy prior to LYFGENIA infusion. At 44-60 months follow up, all five subjects remain transfusion independent without recurrent stroke.

15 REFERENCES

1 Tisdale JF, Pierciey FJ, Bonner M, et al. (2020) Safety and feasibility of hematopoietic progenitor stem cell collection by mobilization with plerixafor followed by apheresis vs bone marrow harvest in patients with sickle cell disease in the multi-center HGB-206 trial. Am J Hematol E239–E242. https://doi.org/10.1002/ajh.25867.
2 Palmer J, McCune JS, Perales M-A, et al. (2016) Personalizing Busulfan-Based Conditioning: Considerations from the American Society for Blood and Marrow Transplantation Practice Guidelines Committee. Biol Blood Marrow Transplant 1915–1925. https://doi.org/10.1016/j.bbmt.2016.07.013
3 Brunson A, Keegan THM, Bang H, et al. (2017) Increased risk of leukemia among sickle cell disease patients in California. Blood 130:1597–1599. doi: 10.1182/blood-2017-05-783233.
4 Seminog OO, Ogunlaja OI, Yeates D, Goldacre MJ (2016) Risk of individual malignant neoplasms in patients with sickle cell disease: English national record linkage study. J R Soc Med 109:303–309. doi: 10.1177/0141076816651037.

16 HOW SUPPLIED/STORAGE AND HANDLING

LYFGENIA is supplied in one to four infusion bags containing a frozen suspension of genetically modified autologous cells, enriched for CD34+ cells. Each bag contains approximately 20 mL. Each infusion bag is individually packed within an overwrap in a metal cassette. LYFGENIA is shipped from the manufacturing facility to the treatment center storage facility in a cryoshipper, which may contain multiple metal cassettes intended for a single patient. A Lot Information Sheet is affixed inside the shipper.

- 20 mL infusion bag, overwrap, and metal cassette (NDC 73554-1111-1)

STORAGE AND HANDLING

Match the identity of the patient with the patient identifiers on the metal cassette(s), infusion bag(s), and Lot Information Sheet upon receipt.

- Keep the infusion bag(s) in the metal cassette(s) and store in the vapor phase of liquid nitrogen at less than or equal to -140°C (≤ -220°F) until ready for thaw and administration.
- Thaw LYFGENIA prior to infusion [see Dosage and Administration (2.2)].
- Do not re-freeze after thawing.
- Do not irradiate LYFGENIA, as this could lead to inactivation.

17 PATIENT COUNSELING INFORMATION

Advise the patient to read the FDA-approved patient labeling (Medication Guide).

Ensure that patients understand the risk of manufacturing failure. In case of manufacturing failure or the need for additional cells, additional cell collection and manufacturing of LYFGENIA would be needed [see Dosage and Administration (2.2)].

Prior to treatment, advise patients of the following:

- Risks associated with mobilization and myeloablative conditioning agents [see Use in Specific Populations (8.1, 8.3)].
- Hematologic Malignancy – Hematologic malignancy has occurred in patients treated with LYFGENIA. Patients with sickle cell disease have an increased risk of hematologic malignancy as compared to the general population. The additional hematopoietic stress associated with mobilization, conditioning, and infusion of LYFGENIA, including the need to regenerate the hematopoietic system, may increase the risk of a hematologic malignancy [see Warnings and Precautions (5.1)].
- Delayed Platelet Engraftment - Delayed platelet engraftment has been observed with LYFGENIA. Patients should be made aware of the risk of bleeding until platelet recovery has been achieved [see Warnings and Precautions (5.2)].
- Risk of Neutrophil Engraftment Failure – Patients who experience neutrophil engraftment failure will receive rescue treatment with their back-up collection of CD34+ cells [see Warnings and Precautions (5.3)].
- Insertional Oncogenesis – There is a potential risk of insertional oncogenesis after treatment with LYFGENIA [see Warnings and Precautions (5.4)].
- Patients should be monitored lifelong. Monitoring will include assessment for hematologic malignancies with a complete blood count at least every 6 months for at least 15 years after treatment with LYFGENIA. This will include integration site analysis at Months 6, 12, and as warranted [see Warnings and Precautions (5.1) and (5.4)].

Advise patients:

- to have their treating physician contact bluebird bio at 1-833-999-6378 if they are diagnosed with a malignancy [see Warnings and Precautions (5.1, 5.4)].
- to monitor for signs and symptoms of bleeding and have frequent blood draws for platelet counts, until platelet recovery has been achieved [see Warnings and Precautions (5.2)].
- that they may test positive for HIV if tested using a PCR assay after being treated with LYFGENIA [see Warnings and Precautions (5.9)].
- that they should not donate blood, organs, tissues, or cells at any time in the future [see Dosage and Administration (2.3)].

Manufactured for:
bluebird bio, Inc.
Somerville, MA 02145

US License No 2160

LYFGENIA is a registered trademark of bluebird bio, Inc.
© bluebird bio, Inc. 2023. All rights reserved.

MEDICATION GUIDE
LYFGENIA® (pronounced lif-JEN-ee-uh)
(lovotibeglogene autotemcel)

What is the most important information I should know about LYFGENIA?
Patients treated with LYFGENIA have developed blood cancers. Treatment with LYFGENIA may increase your risk of developing blood cancer. Blood cancer can develop many years after treatment with LYFGENIA. Blood cancer can be life-threatening and/or cause death.
Because of the risk of blood cancer, you should talk to your doctor about the benefits and risks of LYFGENIA, and about your treatment options. Your doctor may evaluate if you have risk factors that increase your chances of developing blood cancer after LYFGENIA.
Because of the risk of cancer, it is important for you to be monitored at least every 6 months for a minimum of 15 years after LYFGENIA. Monitoring will include blood tests that measure your blood cell counts and evaluation of the blood cells where the gene product is present with specialized tests. If these tests are abnormal, additional testing may be recommended by your doctor. Additional testing might include more frequent blood tests to watch you more closely for changes in your blood. Additional testing could also include a bone marrow evaluation, which can tell your doctor if a blood cancer is developing.
Blood cancer may cause no symptoms, or symptoms can be general. You or your caregiver should call your healthcare provider right away for any of these signs or symptoms:

- Abnormal bruising or bleeding (including nosebleed)
- Blood in urine, stool, or vomit
- Coughing up blood
- Severe headache
- Unusual stomach or back pain
- Fever (100.4°F/38°C or higher)
- Swollen glands
- Abnormal tiredness

If you are diagnosed with a cancer, have your treating physician contact bluebird bio at 1-833-999-6378.
You may experience side effects associated with other medicines administered as part of the LYFGENIA treatment regimen. Talk to your physician regarding those possible side effects. Your healthcare providers may give you other medicines to treat your side effects.
It is important that you or your caregiver tell your healthcare providers that you have received LYFGENIA.

What is LYFGENIA?
LYFGENIA is a one-time gene therapy to treat sickle cell disease. Sickle cell disease is a genetic, inherited, lifelong disease caused by an alteration in one of the genes in the red blood cell, the beta-globin gene, that causes the normal disc-shaped red cells to take the shape of a sickle, causing anemia and vaso-occlusive events, like a pain crisis. LYFGENIA is made specifically for each patient, using the patient's own blood stem cells (from which red blood cells are produced). It adds functional copies of the beta-globin gene to your cells leading to production of anti-sickling hemoglobin that may decrease or stop vaso-occlusive events.

How will I get LYFGENIA?
Before treatment: Your healthcare providers will give you other medicines, including a chemotherapy medicine (given in the vein), as part of your treatment with LYFGENIA. It's important to talk to your healthcare provider about the risks and benefits of all medicines involved in your treatment. You will be admitted to a treatment center during this process (see Step 3).
After receiving the chemotherapy, it may not be possible for you to become pregnant or father a child. You should consider discussing options for fertility preservation with your doctor before treatment.
STEP 1: LYFGENIA is made specifically for you from your own blood stem cells. Your healthcare provider will collect your blood stem cells through a procedure/process called mobilization and apheresis (A-feh-REE-sis). This process takes approximately one week and may need to be repeated to obtain a sufficient number of cells.
'Back-up' stem cells (or 'rescue cells') are also collected and stored at the treatment center. This is a precaution in case there is a problem in the treatment process. If this happens, your back-up stem cells will be given back to you. If you receive back-up cells, you will have no benefit from LYFGENIA.
STEP 2: Your blood stem cells will be sent to a manufacturing site where they are used to make your LYFGENIA. It typically takes 10 to 15 weeks from the time your cells are collected to make and test LYFGENIA before it is shipped to your healthcare provider, but the time may vary.

STEP 3: Before you receive LYFGENIA, your healthcare provider will give you chemotherapy for a few days to make room in the bone marrow. You will be admitted to the treatment center for this step and remain there until after LYFGENIA infusion.

STEP 4: LYFGENIA is given by an intravenous infusion (into your vein). You may receive more than one bag of LYFGENIA. Each bag is infused in 30 minutes or less.
After LYFGENIA infusion, you will stay in the treatment center for approximately 3-6 weeks so that your healthcare team can closely monitor your recovery. Your healthcare provider will determine when you can go home.

What should I avoid after receiving LYFGENIA?

- Do not donate blood, organs, tissues or cells.

What are the possible side effects of LYFGENIA?
The possible side effects of LYFGENIA include:

- On the day of treatment with LYFGENIA
  - Low blood pressure
  - Hot flush
- Following treatment
  - Blood cancer. Refer to "What is the most important information I should know about LYFGENIA?"
  - Longer time for platelets to recover, which may reduce the ability of blood to clot and may cause bleeding

These are not all the possible side effects of LYFGENIA. Call your doctor for medical advice about side effects. You may report side effects to the FDA at 1-800-FDA-1088 or to bluebird bio at 1-833-999-6378.

General information about the safe and effective use of LYFGENIA.
It is important that you have regular check-ups with your healthcare provider, including blood tests at least every 6 months as advised by your health-care provider, to detect any adverse effects and to confirm that LYFGENIA is still working.
Patients treated with LYFGENIA are encouraged to enroll in a post-marketing study to assess the long-term safety of LYFGENIA and the risk of blood cancers occurring after treatment with LYFGENIA. Patients should discuss the option to participate with their physician.
LYFGENIA will not give you a human immunodeficiency virus (HIV) infection. Treatment with LYFGENIA may cause a false-positive HIV test result by some commercial tests (specifically, a PCR-based test). If you need to have an HIV test, talk with your healthcare provider about the appropriate test to use.
Talk to your healthcare provider about any concerns. You can ask your healthcare provider for information about LYFGENIA that is written for healthcare professionals.
For more information, go to LYFGENIA.com or call 1-833-666-2583 for bluebird Patient Services (my bluebird support).
Manufactured for: bluebird bio, Inc., Somerville, Massachusetts 02145

This Medication Guide has been approved by the U.S. Food and Drug Administration.
Issued: December 2023

PRINCIPAL DISPLAY PANEL - 20 mL Bag Patient Identifier Label

lovotibeglogene autotemcel
lyfgenia™

Suspension for IV infusion
20 mL containing 1.7 to 20 x 10^6 cells/mL
(1.4 to 20 x 10^6 CD34+ cells/mL)

Confirm Patient Identifiers

Last Name: $LastName$

First Name: $First Name$

Date of Birth: $DOB$

bbb Patient ID: $bbb_PatientID$

COI ID: $bbb_COI_ID$

LOT: $LOT$

EXP: $Expiry$

Bag X of X

DIN $DIN1_DIN2$

U.S. Lic. # 2160

Label P/N: XXXXXX

bluebirdbio®

PRINCIPAL DISPLAY PANEL - 20 mL Bag Label

lovotibeglogene autotemcel
lyfgenia™

Suspension for IV infusion
20 mL containing 1.7 to 20 x 10^6 cells/mL
(1.4 to 20 x 10^6 CD34+ cells/mL)

For autologous use only. For intravenous use only. Rx only.

Contains genetically modified autologous hematopoietic stem cells
suspended in cryopreservation solution containing 5% DMSO.

Not evaluated for infectious substances.

Do not irradiate. Do not use an in-line blood filter or infusion pump.

See full prescribing information for dosage and administration.

See Lot Information Sheet for number of infusion bags and CD34+
cells per kg for this patient. Dispense with Medication Guide.

P/N: XXXXXXX
Label P/N: XXXXXXX

Manufactured for: bluebird bio, Inc.
Somerville, MA 02145

PRINCIPAL DISPLAY PANEL - 20 mL Bag Cassette Label

lovotibeglogene autotemcel
lyfgenia™

Suspension for IV infusion
20 mL containing 1.7 to 20 x 10^6 cells/mL
(1.4 to 20 x 10^6 CD34+ cells/mL)

For autologous use only. For intravenous use only. Rx only.

Contains genetically modified autologous hematopoietic stem cells
suspended in cryopreservation solution containing 5% DMSO.

Keep infusion bag(s) in the metal cassette(s). Store in the vapor phase of
liquid nitrogen at ≤ -140°C until ready for thaw and administration. Once
thawed do not re-freeze.

See full prescribing information for dosage and administration.

Do not irradiate. Do not use an in-line blood filter or infusion pump.

Not evaluated for infectious substances. No preservatives.

See Lot Information Sheet for number of infusion bags and CD34+ cells
per kg for this patient. Dispense with Medication Guide.

Confirm Patient Identifiers

Last Name: $LastName$

First Name: $FirstName$

Date of Birth: $DOB$

bbb Patient ID: $bbb_PatientID$

COI ID: $bbb_COI_ID$

DIN $DIN1_DIN2$

LOT: $LOT$

EXP: $Expiry$

Bag Xof X

U.S.Lic. # 2160

Manufactured for: bluebird bio, Inc.
Somerville, MA 02145
1-833-999-6378
LYFGENIA.com

P/N: XXXXXXX
Label P/N: XXXXXX

bluebirdbio®